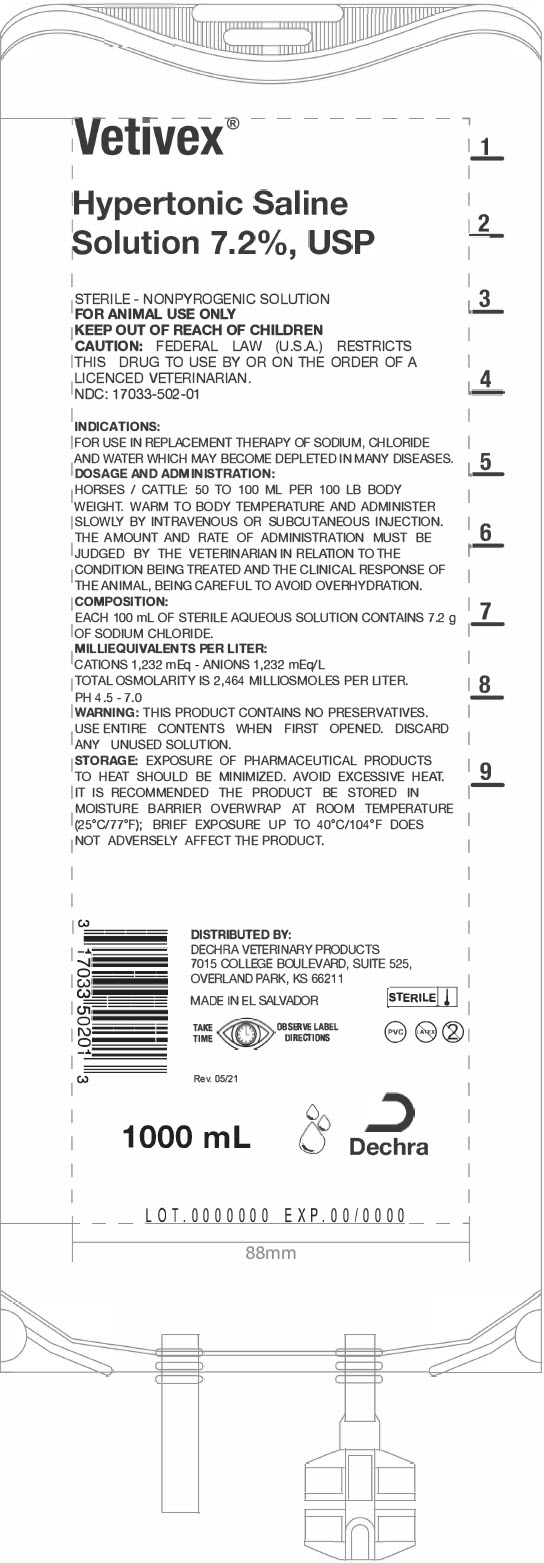 DRUG LABEL: Vetivex 
NDC: 17033-502 | Form: INJECTION, SOLUTION
Manufacturer: Dechra Veterinary Products
Category: animal | Type: PRESCRIPTION ANIMAL DRUG LABEL
Date: 20211119

ACTIVE INGREDIENTS: SODIUM CHLORIDE 7.20 mg/100 mL
INACTIVE INGREDIENTS: WATER

VETIVEX
HYPERTONIC SALINE SOLUTION 7.2%, USP

For Animal Use Only

Description:

Veterinary Hypertonic Saline Solution 7.2%, USP is a sterile, nonpyrogenic solution for fluid and electrolyte replenishment in single dose containers for parenteral administration. It contains no antimicrobial agents. Discard unused portion.

Table 1 Hypertonic saline solution 7.2%, USP
Size (mL) | Sodium Chlorine (mg/mL) | Osmolarity (mEq/L) | pH | Sodium (mEq/L) | Chloride (mEq/L)
1000 | 7200 | 2464 | (4.5 -7.0) | 1232 | 1232

Clinical Pharmacology:

Veterinary Hypertonic saline solutions 7.2%, USP has value as a source of water, electrolytes and calories.

Indications and Usage:

For use in replacement therapy of sodium, chloride and water which may become depleted in many diseases.

Warnings:

This product contains no preservatives. Use entire contents when first opened. Discard any unused solution.

The parenteral administration of Veterinary Hypertonic saline solution 7.2%, USP can cause fluid and/or solute overloading resulting in dilution of serum electrolyte concentrations, overhydration, congested states, or pulmonary edema. The risk of dilutional states is inversely proportional to the electrolyte concentrations of the injections. The risk of solute overload causing congested states with peripheral and pulmonary edema is directly proportional to the electrolyte concentrations of the injection.

In patients with diminished renal function, administration of Veterinary Hypertonic saline solution 7.2%, USP may result in sodium retention.

Adverse reactions:

Reactions which may occur because of the solution or the technique of administration include febrile response, infection at the site of injection, venous thrombosis or phlebitis extending from the site of injection, extravasation, and hypervolemia. If an adverse reaction does occur, discontinue the infusion, evaluate the patient, institute appropriate therapeutic countermeasures, and save the remainder of the fluid for examination if deemed necessary.

Precautions:

Clinical evaluation and periodic laboratory determinations are necessary to monitor changes in fluid balance, electrolyte concentrations, and acid base balance during prolonged parenteral therapy or whenever the condition of the patient warrants such evaluation.

Caution must be exercised in the administration of Veterinary HYPERTONIC SALINE SOLUTION 7.2%, USP to patients receiving corticosteroids or corticotropin. Do not administer unless solution is clear, and seal is intact.

Dosage and administration:

Warm to body temperature and administer slowly by intravenous or subcutaneous injection. The amount and rate of administration must be judged by the veterinarian in relation to the condition being treated and the clinical response of the animal, being careful to avoid overhydration.

Overdosage:

In an event of overhydration or solute overload, re-evaluate the patient and institute appropriate corrective measures.

See Warnings, Adverse Reactions and Precautions.

How Supplied:

HYPERTONIC SALINE SOLUTION 7.2%, USP is supplied in plastic bags as follows:

NDC | Volume
17033-502-01 | 1000 mL

Storage:

Exposure of pharmaceutical products to heat should be minimized. Avoid excessive heat. It is recommended the product be stored in the moisture barrier overwrap at room temperature of (15°C - 30°C) OR (59°F - 86°F). Keep out of reach of children, store between

Directions for use of plastic container

To open:

Tear overwrap downside at slit and remove solution bag. Some opacity of the plastic due to moisture absorption during the sterilization process may be observed. This is normal and does not affect the solution quality or safety. The opacity will diminish gradually. Check for minute leaks by squeezing inner bag firmly. If leaks are found, discard solution as sterility may be impaired. If supplemental medication is desired, follow directions below.

Preparation for Administration:

1. Suspend container from eyelet support.
2. Remove protector from outlet port at bottom of container.
3. Attach administration set. Refer to complete directions accompanying set.

To Add Medication

WARNING: Additives may be incompatible.

To add medication before solution administration:

1. Prepare medication site.
2. Using syringe with 19 to 22-gauge needle, puncture resealable medication port and inject.
3. Mix solution and medication thoroughly. For high density medication such as potassium chloride, squeeze ports while ports are upright and mix thoroughly.

To add medication during solution administration:

1. Close clamp on the administration set to stop the flow to the patient.
2. Prepare medication site.
3. Using syringe with 19 to 22-gauge needle, puncture resealable medication port and inject.
4. Remove container from IV pole and/or turn to an upright position.
5. Evacuate both ports by squeezing them while container is in the upright position.
6. Mix solution and medication thoroughly.
7. Return container to in-use position and continue administration.

CAUTION: Federal law (U.S.A.) restricts this drug to use by or on the order of a licensed veterinarian.

DISTRIBUTED BY:
Dechra Veterinary Products
7015 College Boulevard, Suite 525 Overland Park, KS 66211
Made in El Salvador.
For a copy of the Safety Data Sheet (SDS) or to report adverse reactions call
Dechra Veterinary Products at (866) 933-2472.
© 2021 Dechra Ltd.
Vetivex is a trademark of Dechra Ltd; all rights reserved.
REV07/21

PRINCIPAL DISPLAY PANEL - 1000 mL Container Label

Vetivex®

Hypertonic Saline
Solution 7.2%, USP

STERILE - NONPYROGENIC SOLUTION
FOR ANIMAL USE ONLY
KEEP OUT OF REACH OF CHILDREN
CAUTION: FEDERAL LAW (U.S.A.) RESTRICTS
THIS DRUG TO USE BY OR ON THE ORDER OF A
LICENCED VETERINARIAN.
NDC: 17033-502-01

INDICATIONS:

FOR USE IN REPLACEMENT THERAPY OF SODIUM, CHLORIDE
AND WATER WHICH MAY BECOME DEPLETED IN MANY DISEASES.

DOSAGE AND ADMINISTRATION:

HORSES / CATTLE: 50 TO 100 ML PER 100 LB BODY
WEIGHT. WARM TO BODY TEMPERATURE AND ADMINISTER
SLOWLY BY INTRAVENOUS OR SUBCUTANEOUS INJECTION.
THE AMOUNT AND RATE OF ADMINISTRATION MUST BE
JUDGED BY THE VETERINARIAN IN RELATION TO THE
CONDITION BEING TREATED AND THE CLINICAL RESPONSE OF
THE ANIMAL, BEING CAREFUL TO AVOID OVERHYDRATION.

COMPOSITION:

EACH 100 mL OF STERILE AQUEOUS SOLUTION CONTAINS 7.2 g
OF SODIUM CHLORIDE.

MILLIEQUIVALENTS PER LITER:

CATIONS 1,232 mEq - ANIONS 1,232 mEq/L
TOTAL OSMOLARITY IS 2,464 MILLIOSMOLES PER LITER.
PH 4.5 - 7.0

WARNING: THIS PRODUCT CONTAINS NO PRESERVATIVES.
USE ENTIRE CONTENTS WHEN FIRST OPENED. DISCARD
ANY UNUSED SOLUTION.

STORAGE: EXPOSURE OF PHARMACEUTICAL PRODUCTS
TO HEAT SHOULD BE MINIMIZED. AVOID EXCESSIVE HEAT.
IT IS RECOMMENDED THE PRODUCT BE STORED IN
MOISTURE BARRIER OVERWRAP AT ROOM TEMPERATURE
(25°C/77°F); BRIEF EXPOSURE UP TO 40°C/104°F DOES
NOT ADVERSELY AFFECT THE PRODUCT.

DISTRIBUTED BY:
DECHRA VETERINARY PRODUCTS
7015 COLLEGE BOULEVARD, SUITE 525,
OVERLAND PARK, KS 66211

MADE IN EL SALVADOR
STERILE

TAKE
TIME
OBSERVE LABEL
DIRECTIONS

Rev. 05/21

1000 mL
Dechra

LOT.0000000 EXP.00/0000